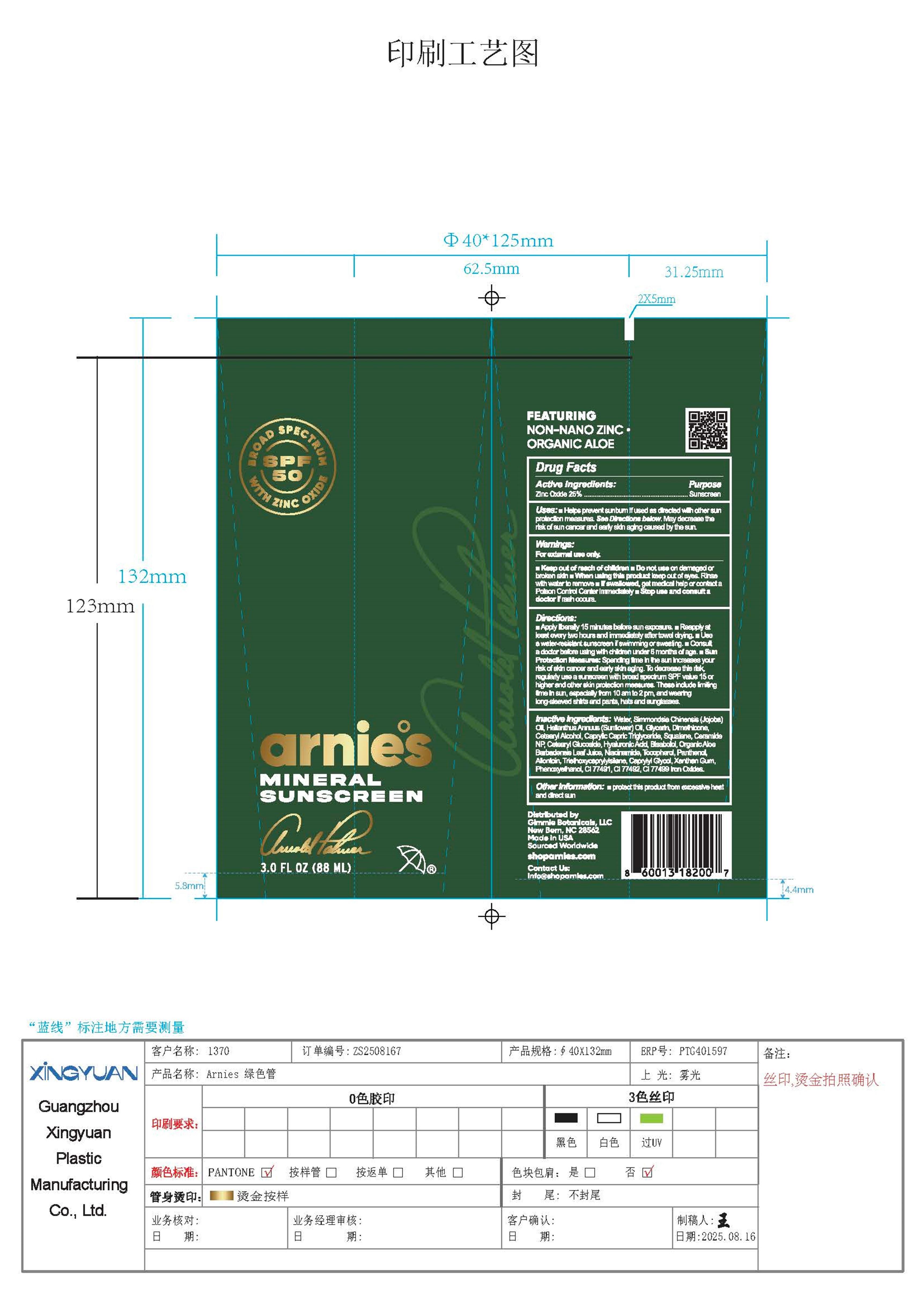 DRUG LABEL: Arnies Mineral Sunscreen - Broad Spectrum SPF 50 with Zinc Oxide
NDC: 87237-001 | Form: CREAM
Manufacturer: Gimmie Botanicals LLC
Category: otc | Type: HUMAN OTC DRUG LABEL
Date: 20251117

ACTIVE INGREDIENTS: ZINC OXIDE 25 g/100 g
INACTIVE INGREDIENTS: CI 77499; WATER; SIMMONDSIA CHINENSIS (JOJOBA) SEED OIL; HELIANTHUS ANNUUS (SUNFLOWER) SEED OIL; GLYCERIN; DIMETHICONE; CETEARYL ALCOHOL; CAPRYLIC/CAPRIC TRIGLYCERIDE; SQUALANE; CERAMIDE NP; CETEARYL GLUCOSIDE; HYALURONIC ACID; BISABOLOL; ALOE BARBADENSIS LEAF JUICE; NIACINAMIDE; TOCOPHEROL; PANTHENOL; ALLANTOIN; CI 77491; CAPRYLYL GLYCOL; PHENOXYETHANOL; CI 77492; TRIETHOXYCAPRYLYLSILANE; XANTHAN GUM

Arnies Mineral Sunscreen - Broad Spectrum SPF 50 with Zinc Oxide

ACTIVE INGREDIENT

Zinc Oxide 25%

PURPOSE

Sunscreen

USE

- Helps prevent sunburn if used as directed with other sun protection measures. See Directions below.
- May decreases the risk of skincancer and early skin aging caused by the sun

WARNINGS

- For external use only
- Do not use on damaged or broken skin
- When using this product keep out of eyes. Rinse with water to remove
- If swallowed, get medical help or contact a Poison Control Center immediately.
- Stop use and consult a doctor if rash occurs.

KEEP OUT OF REACH OF CHILDREN

DIRECTIONS

- Apply liberal / 15 minutes before sun exposure.
- Reapply at least every two hours and immediately after towel drying.
- Use a water-resistant sunscreen if swimming or sweating.
- Consult a doctor before using with children under 6 months of age.
- Sun Protection Measures: Spending time in the sun increases your risk of skin cancer and early skin aging. To decrease this risk, regularly use a sunscreen with broad spectrum SPF value 15 or higher and other skin protection measures. These include limiting time in sun, especially from 10 am to 2 pm, and wearing long-sleeved shirts and pants, hats and sunglasses.

INACTIVE INGREDIENTS

Water, Simmondsia Chinensis (Jojoba) Oil, Helianthus Annuus (Sunflower) Oil, Glycerin, Dimethicone, Cetearyl Alcohol, Caprylic Capric Triglyceride, Squalane, Ceramide NP, Cetearyl Glucoside, Hyaluronic Acid, Bisabolol, Organic Aloe Barbadensis Leaf Juice, Niacinamide, Tocopherol, Panthenol, Allantoin, Triethoxycaprylylsilane, Caprylyl Glycol, Xanthan Gum, Phenoxyethanol, CI 77491, CI 77492, and CI 77499 Iron Oxides.